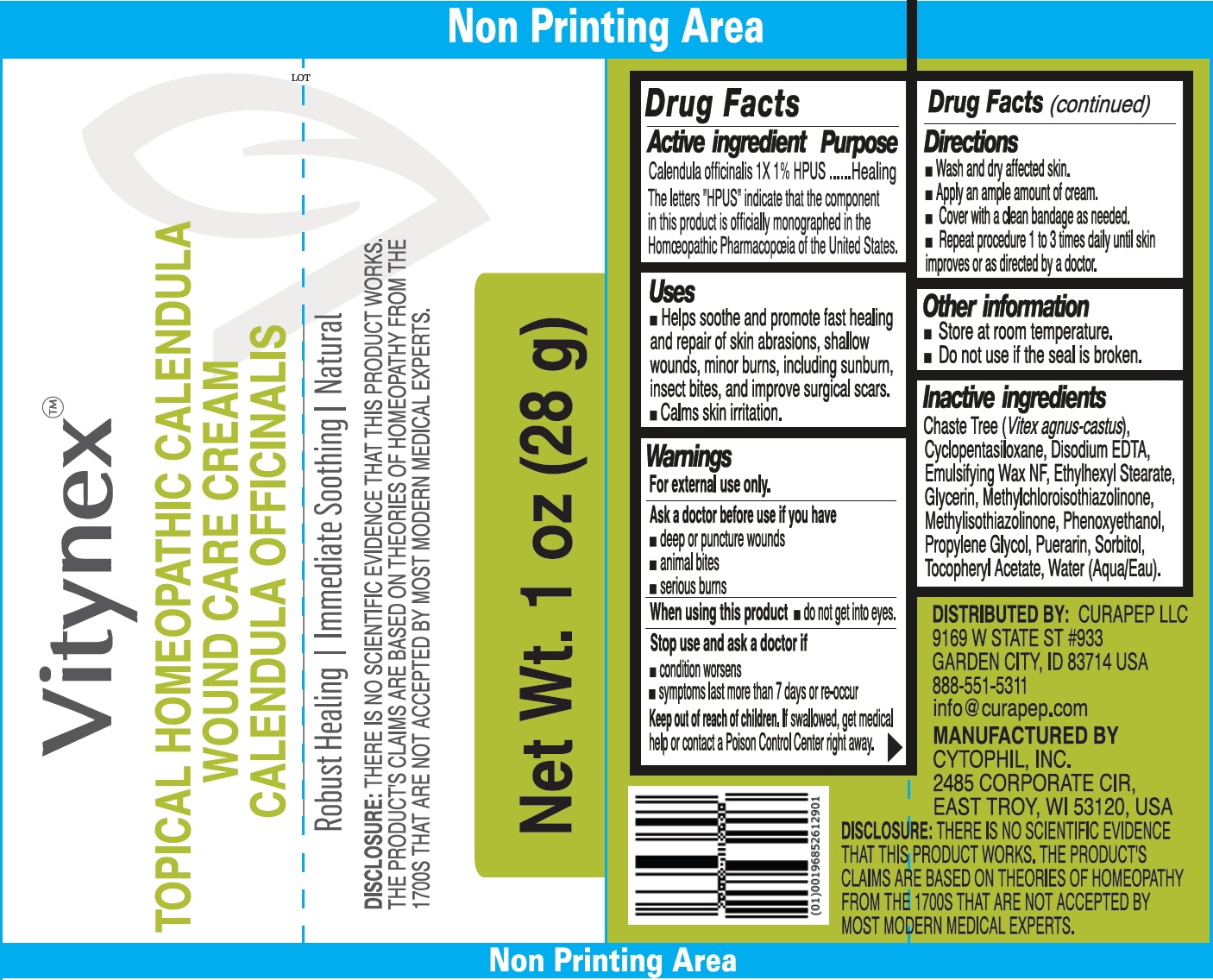 DRUG LABEL: Vitynex Topical Homeopathic Calendula Wound Care
NDC: 84337-001 | Form: CREAM
Manufacturer: CuraPep
Category: homeopathic | Type: HUMAN OTC DRUG LABEL
Date: 20240626

ACTIVE INGREDIENTS: CALENDULA OFFICINALIS FLOWERING TOP 1 [hp_X]/1 g
INACTIVE INGREDIENTS: CHASTE TREE FRUIT; CYCLOMETHICONE 5; EDETATE DISODIUM; ETHYLHEXYL STEARATE; GLYCERIN; METHYLCHLOROISOTHIAZOLINONE; METHYLISOTHIAZOLINONE; PHENOXYETHANOL; PROPYLENE GLYCOL; PUERARIN; SORBITOL; .ALPHA.-TOCOPHEROL ACETATE; WATER

Vitynex Topical Homeopathic Calendula Wound Care Cream

Active ingredient

Calendula officinalis 1X 1% HPUS

The letters "HPUS" indicate that the component in this product is officially monographed in the Homoeopathic Pharmacopoeia of the United States.

Purpose

Healing

Uses

- Helps soothe and promote fast healing and repair of skin abrasions, shallow wounds, minor burns, including sunburn, insect bites, and improve surgical scars.
- Calms skin irritation.

Warnings

For external use only.

Ask a doctor before use if you have

- deep or puncture wounds
- animal bites
- serious burns

When using this product

- do not get into eyes.

Stop use and ask a doctor if

- condition worsens
- symptoms last more than 7 days or re-occur

Keep out of reach of children.

If swallowed, get medical help or contact a Poison Control Center right away.

Directions

- Wash and dry affected skin.
- Apply an ample amount of cream.
- Cover with a clean bandage as needed.
- Repeat procedure 1 to 3 times daily until skin improves or as directed by a doctor.

Other information

- Store at room temperature.
- Do not use if the seal is broken.

Inactive ingredients

Chaste Tree (Vitex agnus-castus), Cyclopentasiloxane, Disodium EDTA, Emulsifying Wax NF, Ethylhexyl Stearate, Glycerin, Methylchloroisothiazolinone, Methylisothiazolinone, Phenoxyethanol, Propylene Glycol, Puerarin, Sorbitol, Tocopheryl Acetate, Water (Aqua).